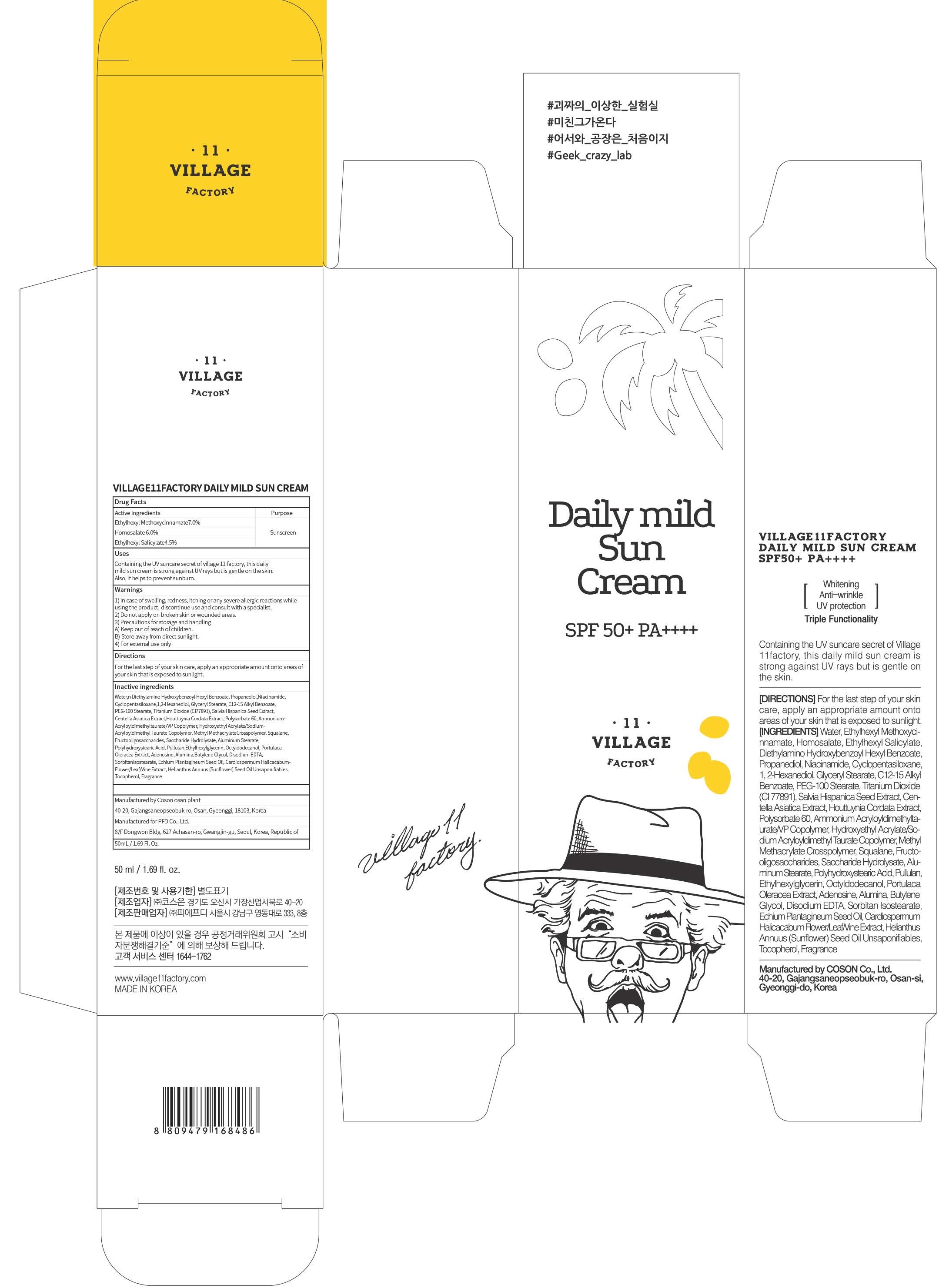 DRUG LABEL: VILLAGE11FACTORY DAILY MILD SUN
NDC: 72470-010 | Form: CREAM
Manufacturer: PFD Co.,Ltd.
Category: otc | Type: HUMAN OTC DRUG LABEL
Date: 20180807

ACTIVE INGREDIENTS: Octinoxate 3.50 g/50 mL; Homosalate 3.00 g/50 mL; Octisalate 2.25 g/50 mL
INACTIVE INGREDIENTS: Water; Niacinamide

ACTIVE INGREDIENT

Active ingredients: Ethylhexyl Methoxycinnamate 7.0%, Homosalate 6.0%, Ethylhexyl Salicylate 4.5%

INACTIVE INGREDIENT

Inactive ingredients:

Water,n Diethylamino Hydroxybenzoyl Hexyl Benzoate, Propanediol,Niacinamide, Cyclopentasiloxane,1,2-Hexanediol, Glyceryl Stearate, C12-15 Alkyl Benzoate,PEG-100 Stearate, Titanium Dioxide (CI77891), Salvia Hispanica Seed Extract, Centella Asiatica Extract,Houttuynia Cordata Extract, Polysorbate 60, AmmoniumAcryloyldimethyltaurate/VP Copolymer, Hydroxyethyl Acrylate/Sodium Acryloyldimethyl Taurate Copolymer, Methyl MethacrylateCrosspolymer, Squalane,Fructooligosaccharides, Saccharide Hydrolysate, Aluminum Stearate, Polyhydroxystearic Acid, Pullulan,Ethylhexylglycerin, Octyldodecanol, Portulaca Oleracea Extract, Adenosine, Alumina,Butylene Glycol, Disodium EDTA, SorbitanIsostearate, Echium Plantagineum Seed Oil, Cardiospermum Halicacabum Flower/Leaf/Vine Extract, Helianthus Annuus (Sunflower)Seed Oil Unsaponifiables, Tocopherol, Fragrance

PURPOSE

Purpose: Sunscreen

WARNINGS

1) In case of swelling, redness, itching or any severe allergic reactions while using the product, discontinue use and consult with a specialist.

2) Do not apply on broken skin or wounded areas.

3) Precautions for storage and handling A) Keep out of reach of children. B) Store away from direct sunlight.

4) For external use only

DESCRIPTION

Uses:

Containing the UV suncare secret of village 11 factory, this daily mild sun cream is strong against UV rays but is gentle on the skin. Also, it helps to prevent sunburn.

Directions:

For the last step of your skin care, apply an appropriate amount onto areas of your skin that is exposed to sunlight.